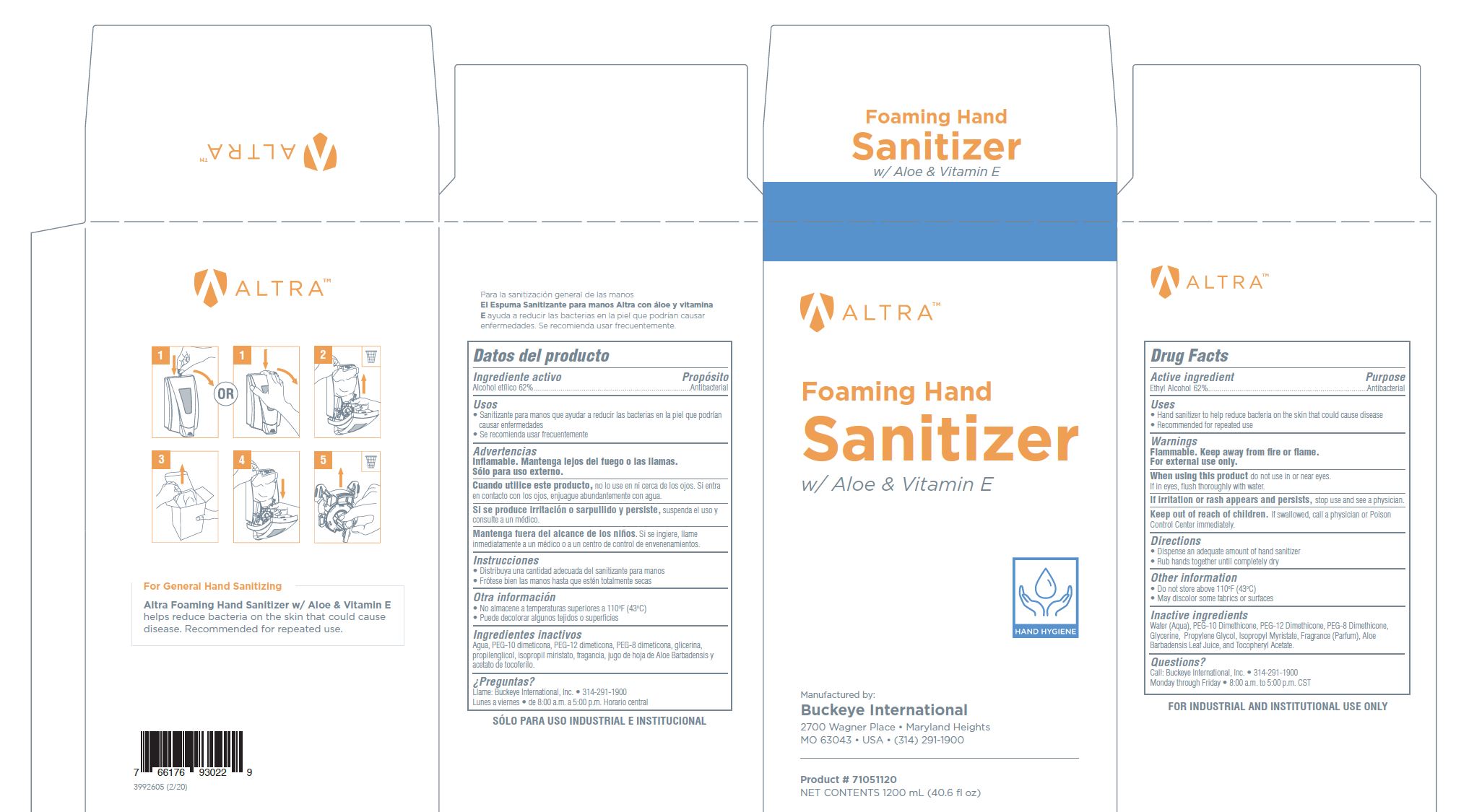 DRUG LABEL: Altra Foaming Hand Sanitizer with Aloe and Vitamin E
NDC: 30805-012 | Form: SOLUTION
Manufacturer: Buckeye International, Inc.
Category: otc | Type: HUMAN OTC DRUG LABEL
Date: 20250325

ACTIVE INGREDIENTS: ALCOHOL 62 mL/100 mL
INACTIVE INGREDIENTS: PEG-12 DIMETHICONE (300 CST); PEG-8 DIMETHICONE; GLYCERIN; PROPYLENE GLYCOL; ALOE VERA LEAF; WATER; ISOPROPYL MYRISTATE; PEG-10 DIMETHICONE (600 CST); .ALPHA.-TOCOPHEROL ACETATE

Drug Facts
30805-012

Active ingredient

Ethyl Alcohol 62%

Purpose

Antibacterial

Uses

- Hand sanitizer to help reduce bacteria on the skin that could cause disease
- Recommended for repeated use

Warnings

Flammable, Keep away from fire or flame.

For external use only.

WHEN USING

When using this productdo not use in or near eyes.

If in eyes, flush thoroughly with water.

STOP USE

If irritation or rash appears and persists, stop use and see a physician.

Keep out of reach of children.If swallowed, call a physician or Poison Control Center immediately

Directions

- Dispense an adequate amount of hand sanitizer
- Rub hands together until completely dry

Other information

- Do not store above 110 F (43 C)
- May discolor some fabrics or surfaces

Inactive ingredients

Water (Aqua), PEG-10 Dimethicone, PEG-12 Dimethicone, PEG-8 Dimethicone, Glycerine, Propylene Glycol, Isopropyl Myristate, Fragrance (parfum), Aloe Barbadesis Leaf Juice and Tocopheryl Acetate.

Questions?

Call Buckeye International, Inc. 314-291-1900

Monday through Friday 8:00 a.m. to 5:00p.m. CST

PACKAGE LABEL

ALTRA

Foaming Hand

Sanitizer

with Aloe and Vitamin E

Hand Hygiene

Manufacteyred By

Buckeye International

2700 Wagner Place Maryland Heights

MO 63043 USA (314) 291-1900

Product # 71051120

Net Contents 1200 mL (40.6 fl oz)